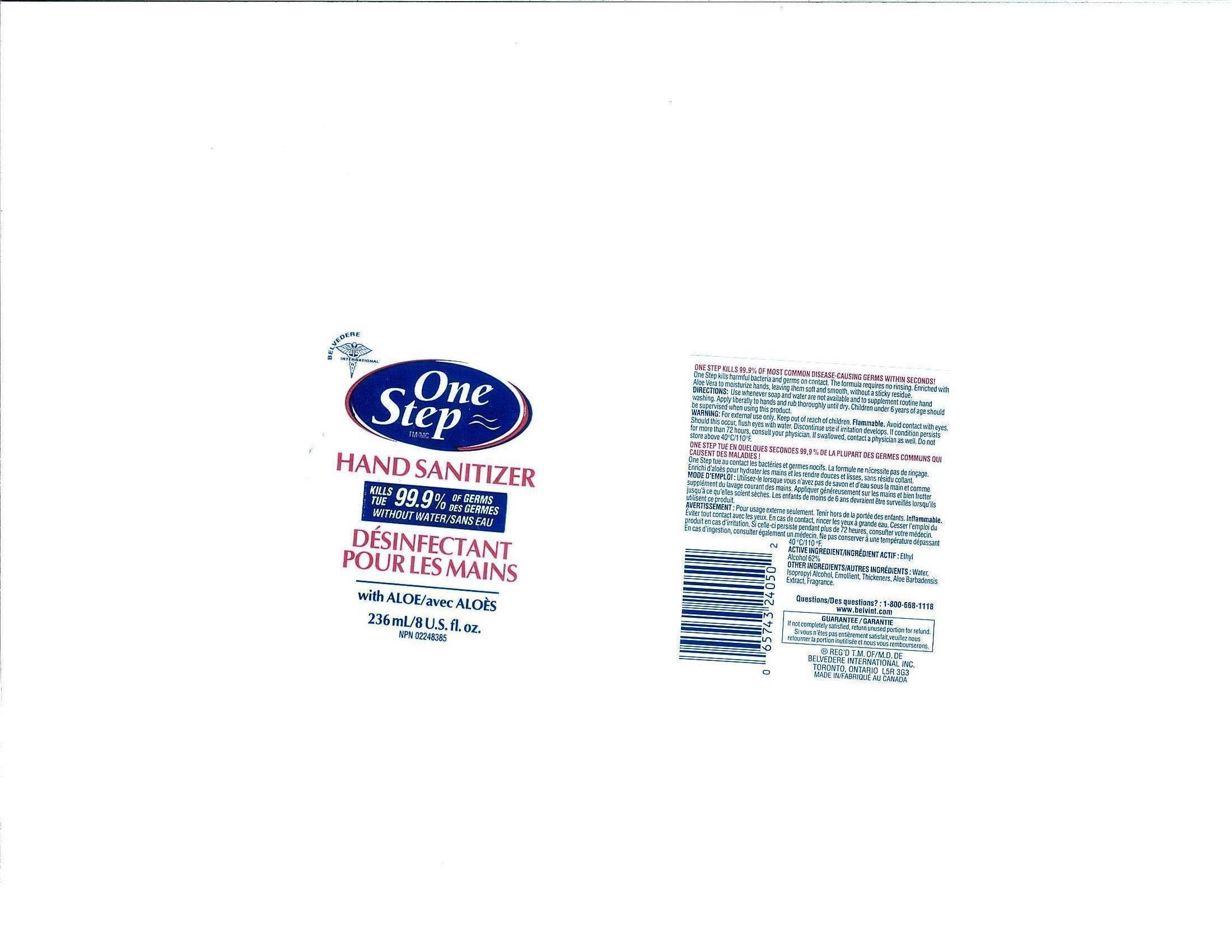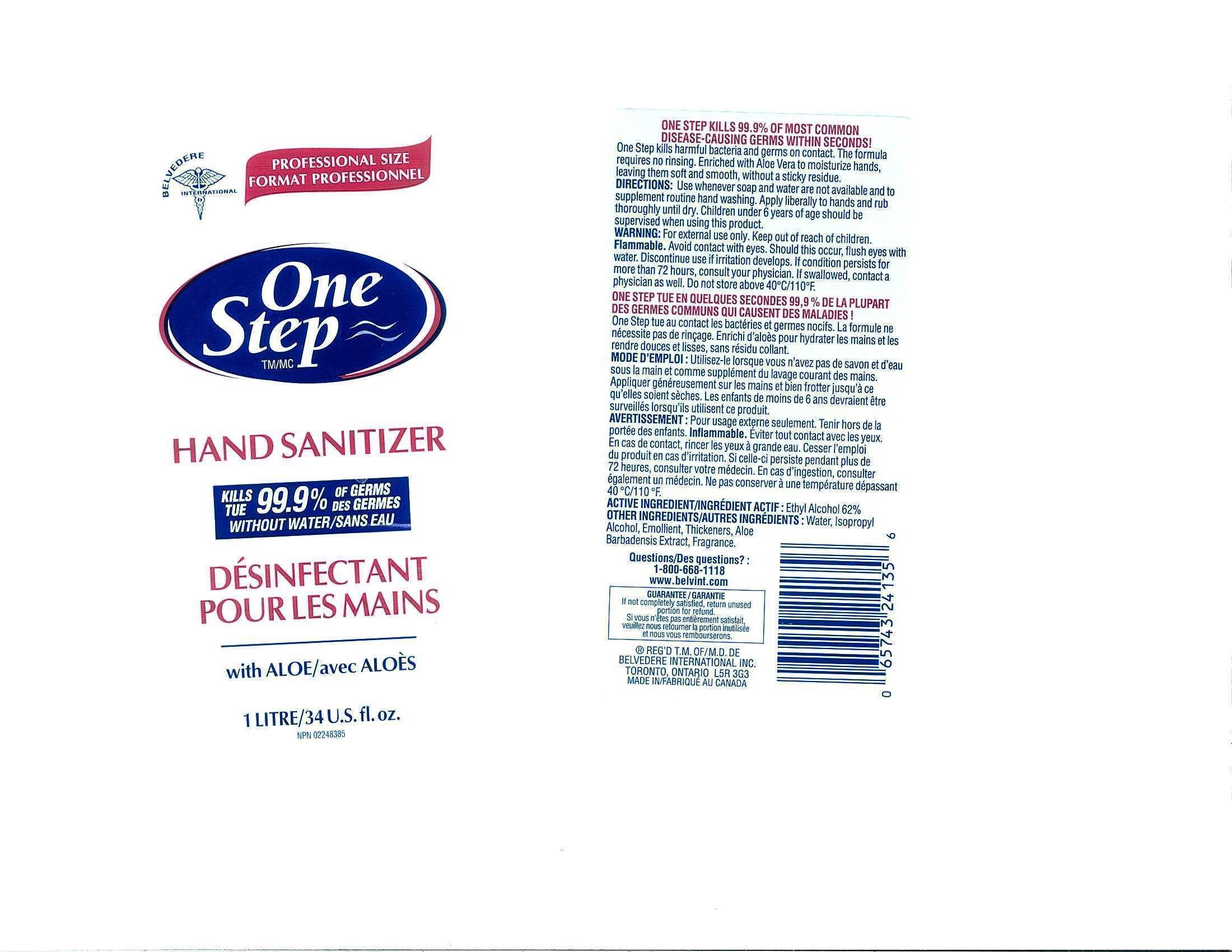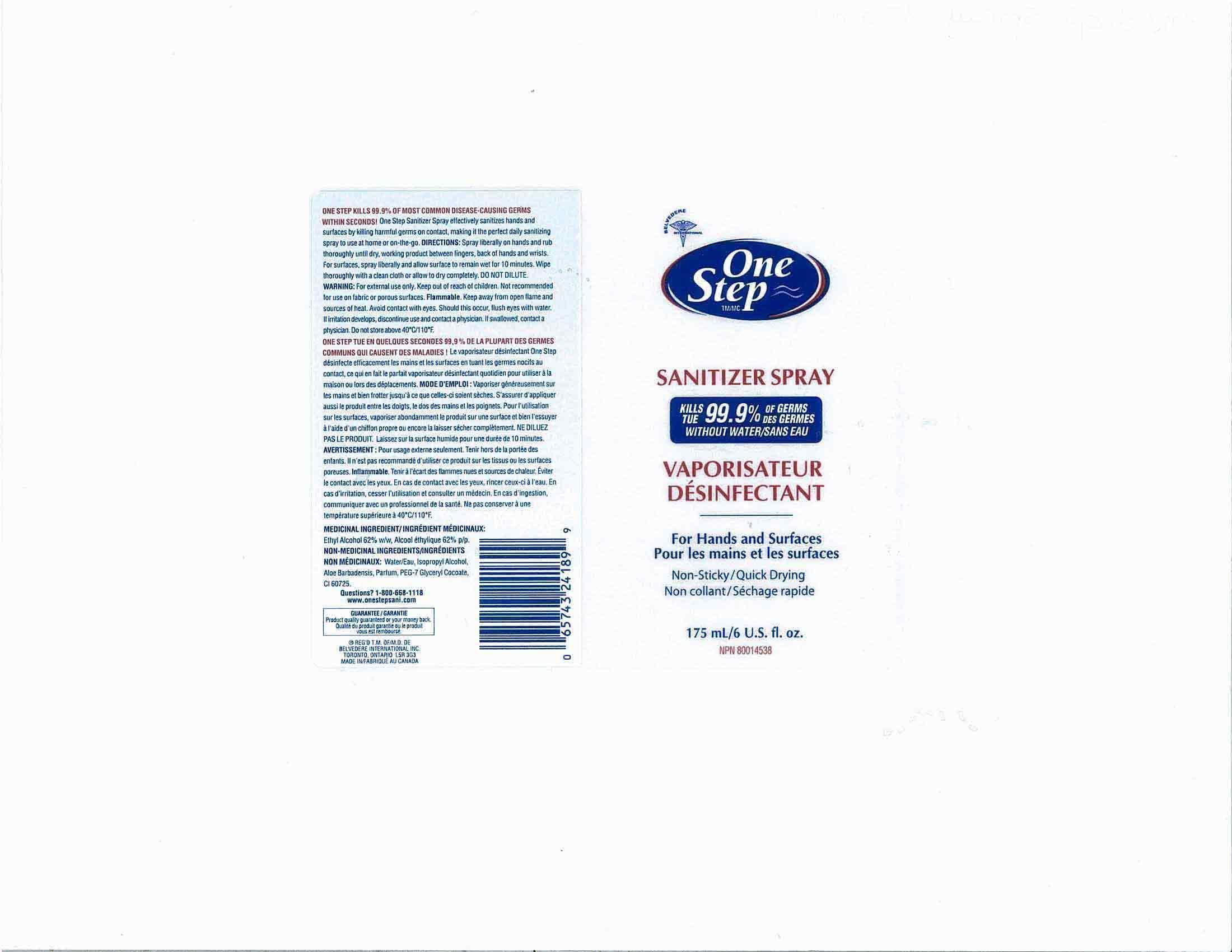 DRUG LABEL: One Step Hand Sanitizer Aloe
NDC: 60742-001 | Form: GEL
Manufacturer: BELVEDERE INTERNATIONAL INC.
Category: otc | Type: HUMAN OTC DRUG LABEL
Date: 20130911

ACTIVE INGREDIENTS: ALCOHOL 62 mL/100 mL
INACTIVE INGREDIENTS: WATER; POLYSORBATE 20; ALOE VERA LEAF; CARBOMER 934; ISOPROPYL ALCOHOL

DRUG FACTS

DRUG FACTS

Active Ingredient

Ethyl Alcohol 62%

PURPOSE

USE WHENEVER SOAP AND WATER ARE NOT AVAILABLE AND TO SUPPLEMENT ROUTING HAND WASHING

KEEP OUT OF REACH OF CHILDREN

CHILDREN UNDER 6 YEARS OF AGE SHOULD BE SURPERVISED WHEN USING THIS PRODUCT, KEEP OUT OF REACH OF CHILDREN

INDICATIONS AND USAGE

USE WHENEVER SOAP AND WATER ARE NOT AVAILABLE AND TO SUPPLEMENT ROUTINE HAND WASHING, APPLY LIBERALLY TO HAND AND RUB THOROUGHLY UNTIL DRY

WARNINGS

FOR EXTERNAL USE ONLY, KEEP OUT OF REACH OF CHILDREN, FLAMMABLE, AVOID CONTACT WITH EYES SHOULD THIS OCCUR FLUSH WITH WATER DISCONTINUE USE IF IRRITATION DEVELOPS, IF CONDITION PERSISTS FOR MORE THAN 72 HOURS CONSULT YOUR PHYSICIAN. IF SWALLOWED CONTACT A PHYSICIAN AS WELL, DO NO STORE ABOVE 40^0 C/110^0F

DOSAGE AND ADMINISTRATION

APPLY LIBERALLY TO HAND AND RUB THOROUGHLY UNTIL DRY

INACTIVE INGREDIENT

WATER, ISOPROPYL ALCOHOL, CARBOMER, ALOE VERA LEAF, POLYSORBATE 20, PARFUM